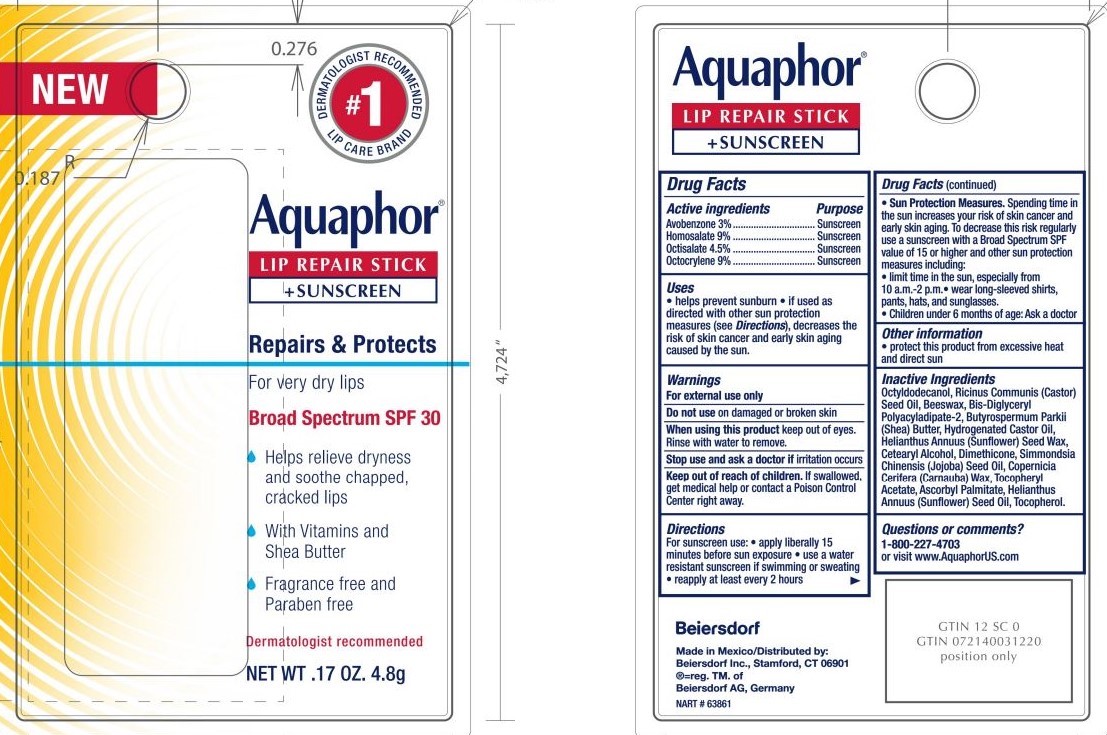 DRUG LABEL: Aquaphor Lip Repair Stick and Sunscreen
NDC: 10356-130 | Form: STICK
Manufacturer: Beiersdorf Inc
Category: otc | Type: HUMAN OTC DRUG LABEL
Date: 20251216

ACTIVE INGREDIENTS: OCTISALATE 4.5 g/100 g; AVOBENZONE 3 g/100 g; OCTOCRYLENE 9 g/100 g; HOMOSALATE 9 g/100 g
INACTIVE INGREDIENTS: HELIANTHUS ANNUUS SEED WAX; CETOSTEARYL ALCOHOL; HYDROGENATED CASTOR OIL; CARNAUBA WAX; ASCORBYL PALMITATE; SHEA BUTTER; BIS-DIGLYCERYL POLYACYLADIPATE-2; .ALPHA.-TOCOPHEROL ACETATE; TOCOPHEROL; DIMETHICONE; OCTYLDODECANOL; CASTOR OIL; YELLOW WAX; JOJOBA OIL

Aquaphor Lip Repair Stick + Sunscreen

Active ingredients:

Avobenzone 3%

Homosalate 9%

Octisalate 4.5%

Octocrylene 9%

Purpose:

Sunscreen

INDICATIONS AND USAGE

Uses • helps prevent sunburn • if used as directed with other sun protection measures (see Directions), decreases the risk of skin cancer and early skin aging caused by the sun

Warnings:

For external use only

Do not use on damaged or broken skin

When using this product, keep out of eyes. Rinse with water to remove.

Stop use and ask a doctor if rash occurs

Keep out of reach of children. If swallowed, get medical help or contact a
Poison Control Center right away

DOSAGE AND ADMINISTRATION

For sunscreen use

- apply liberally at least 15 minutes before sun exposure
- use a water resistant sunscreen if swimming or sweating
- reapply at least every two hours
- Sun Protection Measures. Spending time in the sun increases your risk of skin cancer and early skin aging. To decrease this risk regularly use a sunscreen with a Broad SpectrumSPFvalue of 15 or higher and other sun protection measures including: •limit time in the sun, especially from 10 a.m. – 2 p.m. •wear long-sleeved shirts, pants, hats, and sunglasses
- children under 6 months of age: Ask a doctor

Inactive ingredients
Octyldodecanol, Ricinus Communis (Castor) Seed Oil, Beeswax, Bis-Diglyceryl Polyacyladipate-2, Butyrospermum Parkii (Shea) Butter, Hydrogenated Castor OIl, Helianthus Annuus (Sunflower) Seed Wax, Cetearyl Alcohol, Dimethicone, Simmondsia Chinensis (Jojoba) Seed Oil, Copernicia Cerifera (Carnauba) Wax, Tocopheryl Acetate, Ascorbyl Palmitate, Tocopherol.

Questions? 1-800-227-4703

PACKAGE LABEL

Aquaphor Lip Repair Stick

+ Sunscreen

#1 Dermatologist Recommended Lip Care Brand

Repairs and Protects

For very dry lips

Broad spectrum SPF 30

Helps relieve dryness and soothe cracked, chapped lips

With Vitamins and Shea Butter

Fragrance Free and Paraben Free

Dermatologist recommended